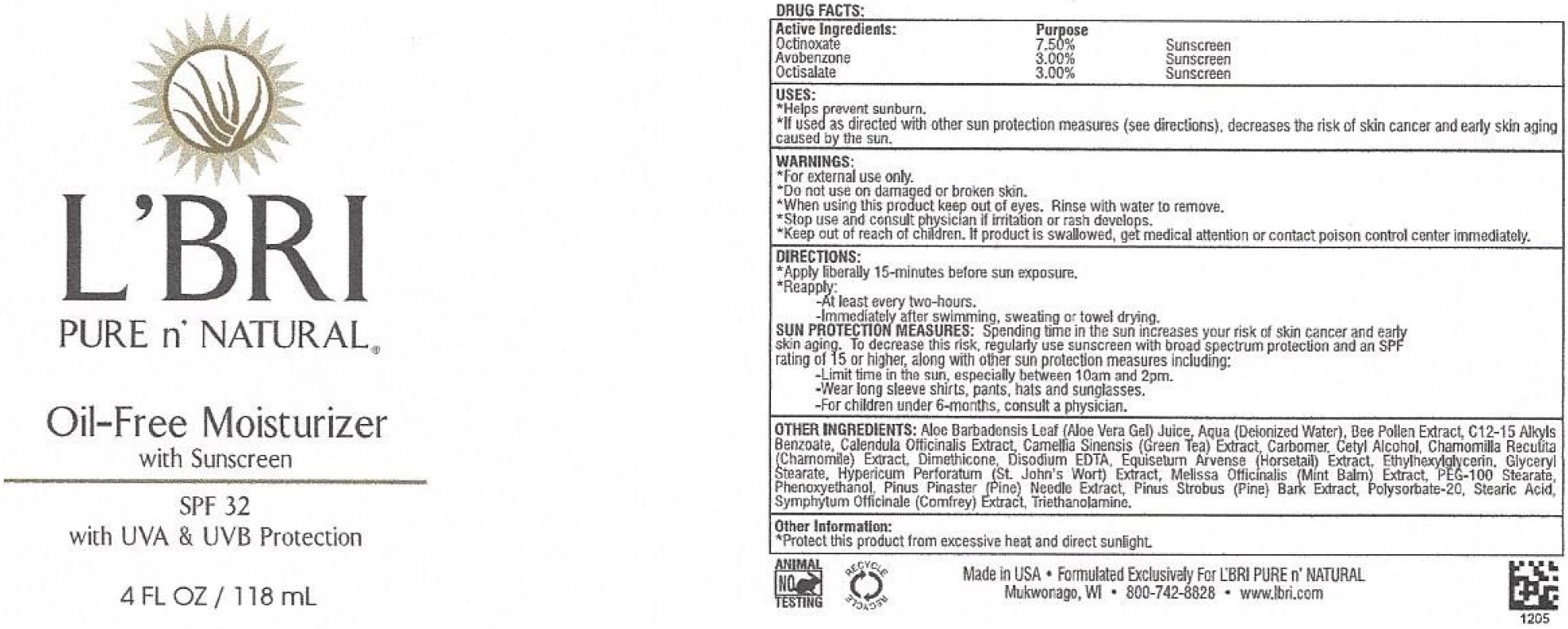 DRUG LABEL: LBri Pure nNatural Oil Free Moisturizer
NDC: 71238-785 | Form: CREAM
Manufacturer: L'Bri Health & Beauty
Category: otc | Type: HUMAN OTC DRUG LABEL
Date: 20231111

ACTIVE INGREDIENTS: OCTINOXATE 75 mg/1 mL; AVOBENZONE 30 mg/1 mL; OCTISALATE 30 mg/1 mL
INACTIVE INGREDIENTS: ALOE VERA LEAF; WATER; ALKYL (C12-15) BENZOATE; CALENDULA OFFICINALIS FLOWER; GREEN TEA LEAF; CARBOXYPOLYMETHYLENE; CETYL ALCOHOL; CHAMOMILE; DIMETHICONE; EDETATE DISODIUM ANHYDROUS; EQUISETUM ARVENSE BRANCH; ETHYLHEXYLGLYCERIN; GLYCERYL MONOSTEARATE; HYPERICUM PERFORATUM; MELISSA OFFICINALIS; PEG-100 STEARATE; PHENOXYETHANOL; PINUS STROBUS BARK; POLYSORBATE 20; STEARIC ACID; TROLAMINE

L'Bri Pure n'Natural Oil-Free Moisturizer SPF-32

Active Ingredients:

Octinoxate 7.50%

Avobenzone 3.00%

Octisalate 3.00%

Purpose

Sunscreen

USES:

- Helps prevent sunburn.
- If used as directed with other sun protection measures (see directions), decreases the risk of skin cancer and early skin aging caused by the sun.

WARNINGS:

- For external use only.

Do not use

on damaged or broken skin.

When using this product keep out of eyes.

Rinse with water to remove.

Stop use and consult physician

if irritation or rash develops.

Keep out of reach of children.

If product is swallowed, get medical attention or contact poison control center immediately.

DIRECTIONS:

- Apply liberally 15-minutes before sun exposure.
- Reapply:

- Limit time in the sun, especially between 10am and 2pm.
- Wear long sleeve shirts, pants, hats and sunglasses.
- For children under 6-months, consult a physician.

-At least every two-hours.

Immediately after swimming, sweating or towel drying.

SUN PROTECTION MEASURES: Spending time in the sun increases your risk of skin cancer and early skin aging. To decrease this risk, regularly use sunscreen with broad spectrum protection and an SPF rating of 15 or higher, along with other sun protection measures including:

OTHER INGREDIENTS:

Aloe Barbadensis Leaf (Aloe Vera Gel) Juice, Aqua (Deionized Water), Bee Pollen Extract, C12-15 Alkyls Benzoate, Calendula Officinalis Extract, Camellia Sinensis (Green Tea) Extract, Carbomer, Cetyl Alcohol, Chamomilla Recutita (Chamomile) Extract, Dimethicone, Disodium EDTA, Equisetum Arvense (Horsetail) Extract, Ethylhexylglycerin, Glyceryl Stearate, Hypericum Perforatum (St. John's Wort) Extract, Melissa Officinalis (Mint Balm) Extract, PEG-100 Stearate, Phenoxyethanol, Pinus Pinaster (Pine) Needle Extract, Pinus Strobus (Pine) Bark Extract, Polysorbate-20, Stearic Acid, Symphytum Officinale (Comfrey) Extract, Triethanolamine.

Other Information:

- Protect this product from excessive heat and direct sunlight.